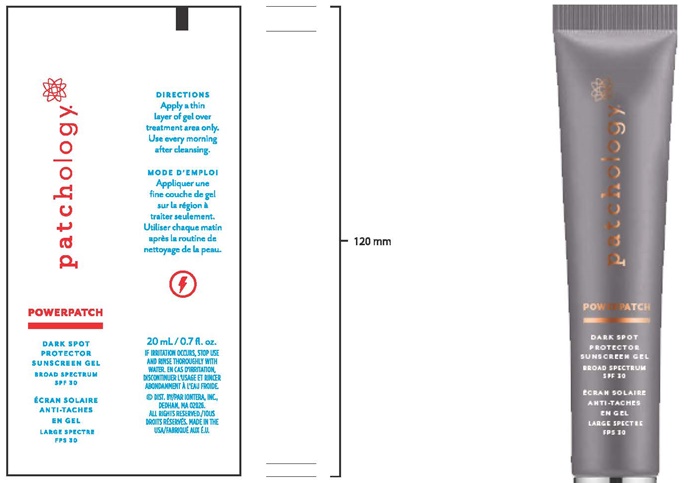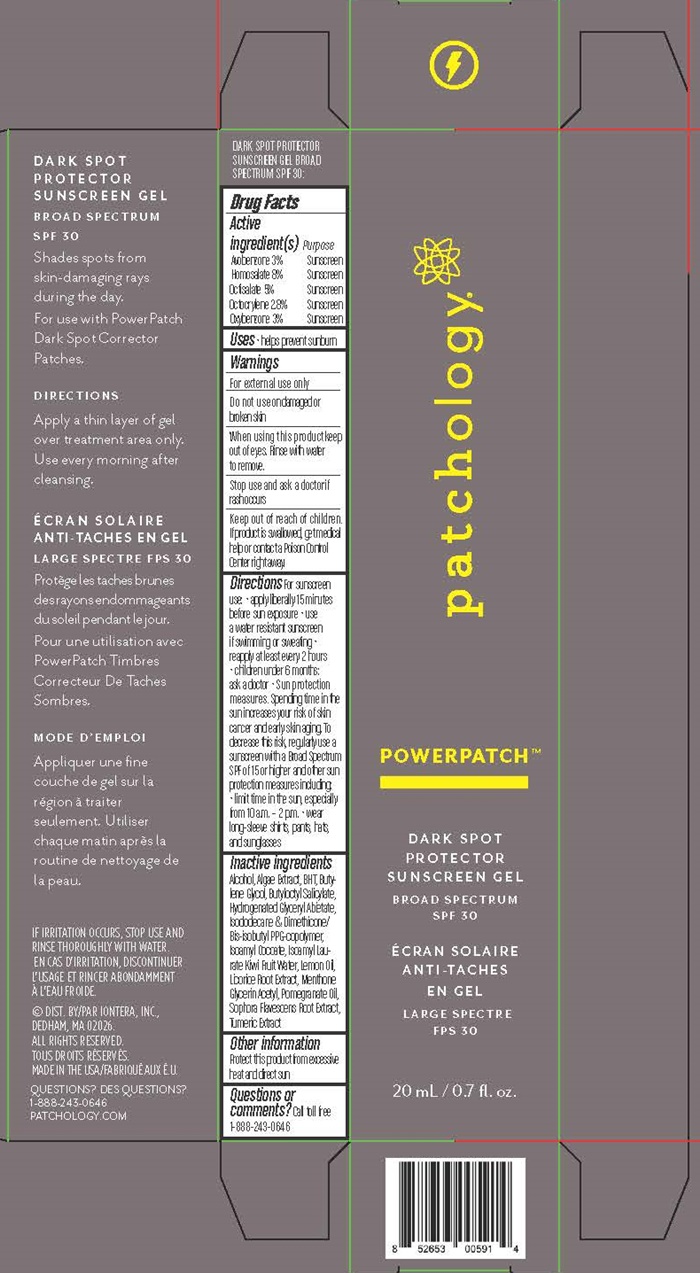 DRUG LABEL: PowerPatch Dark Spot Protector
NDC: 65692-0588 | Form: GEL
Manufacturer: Raining Rose
Category: otc | Type: HUMAN OTC DRUG LABEL
Date: 20160722

ACTIVE INGREDIENTS: AVOBENZONE 0.6 g/20 mL; HOMOSALATE 1.6 g/20 mL; OCTISALATE 1.0 g/20 mL; OCTOCRYLENE 0.56 g/20 mL; OXYBENZONE 0.6 g/20 mL
INACTIVE INGREDIENTS: ALCOHOL; LAMINARIA ANGUSTATA; BUTYLATED HYDROXYTOLUENE; BUTYLENE GLYCOL; BUTYLOCTYL SALICYLATE; GLYCERYL ABIETATE; ISODODECANE; DIMETHICONE/BIS-ISOBUTYL PPG-20 CROSSPOLYMER; ISOAMYL COCOATE; ISOAMYL LAURATE; KIWI FRUIT; LEMON OIL; LICORICE; MENTHONE 1,2-GLYCEROL KETAL, (+/-)-; POMEGRANATE SEED OIL; SOPHORA FLAVESCENS ROOT; TURMERIC

RR Dark Spot Corrector - 0588

DARK SPOT PROTECTIOR SUNSCREEN GEL BROAD SPECTRUM SPF 30: Drug Facts Active ingredient(s)

Avobenzone 3%

Homosalate 8%

Octisalate 5%

Octocrylene 2.8%

Oxybenzone 3%

Purpose

Sunscreen

Keep out of reach of children

If swallowed, get medical help or contact a Poison Control Center right away.

Uses

- helps prevent sunburn

Warnings

For external use only

Do not use

on damaged or broken skin

When using this product

keep out of the eyes. Rinse with water to remove.

Stop use and ask a doctor

if rash occurs

Directions

For sunscreen use

- apply liberally 15 minutes before sun exposure
- use a water resistant sunscreen if swimming or sweating
- reapply at least every 2 hours
- children under 6 months ask a doctor

Sun protection measures

Spending time in the sun increases your risk of skin cancer and early skin aging. To decrease this risk, regularly use a sunscreen with a Broad Spectrum SPF of 15 or higher and other sun protection measures including:

- limit time in the sun, especially from 10 a.m. - 2 p.m.
- wear long-sleeve shirts, pants, hats, and sunglasses

Inactive ingredients

Alcohol, Algae Extract, BHT, Butylene Glycol, Butyloctyl Salicylate, Hydrogenated Glyceryl Abietate, Isododecane & Dimethicone/Bis-isobutyl PPG-copolymer, Isoarryl Cocoate, Isoamyl Laurate, Kiwi fruit Water, Lemon Oil, Licorice Root Extract, Menthone Glycerin Acetyl, Pomegranate Oil, Sophora Flavescens Root Extract, Tumeric Extract

Other information

Protect this product from excessive heat and direct sun

Questions or comments?

Call toll free 1-888-243-0646

Dark Spot Corrector product label

patchology®

POWERPATCH™

DARK SPOT PROTECTOR
SUNSCREEN GEL
BROAD SPECTRUM SPF 30

20 mL

DARK SPOT PROTECTOR SUNSCREEN GEL

BROAD SPECTRUM SPF 30

Shades spots from skin-damaging rays during the day.

For use withPowerPatch Dark Spot Corrector Patches.

DIRECTIONS

Apply a thin layer of gel over treatment area only. Use every morning after cleansing.

IF IRRITATION OCCURS, STOP USE AND RINSE THOROUGHLY WITH WATER.

DIST. BY/PAR IONTERA, INC.,

DEDHAM, MA 02026
ALL RIGHTS RESERVED
MADE IN THE USA

QUESTIONS?
1-888-243-0646
PATCHOLOGY.COM